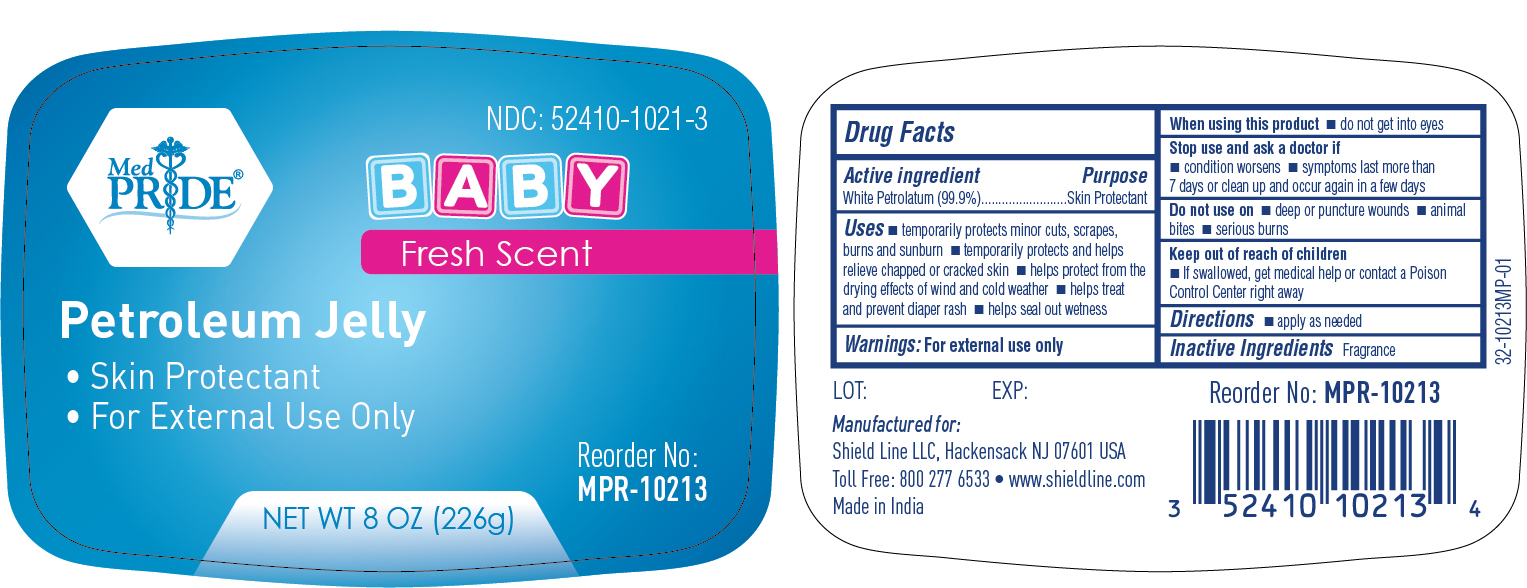 DRUG LABEL: Novita Baby Petrolatum Jelly
NDC: 52410-1021 | Form: JELLY
Manufacturer: Shield Line LLC
Category: otc | Type: HUMAN OTC DRUG LABEL
Date: 20250818

ACTIVE INGREDIENTS: PETROLATUM 99.9 g/100 g
INACTIVE INGREDIENTS: WATER

Active Ingredient

White Petrolatum (99.9% w/w)

Purpose

Skin Protectant

Uses

- temporarily protects minor cuts, scrapes, burns and sunburn
- temporarily protects and helps relieve chapped or cracked skin
- helps protect from drying effect of wind and cold weather
- helps treat and prevent diaper rash
- help seal out wetness

Warnings

FOR EXTERNAL USE ONLY

When using this product

- do not get into the eyes

Stop use and ask a doctor if

- condition worsens
- symptoms last for more than 7 days or clean up and occur again in a few days

Do not use on

- deep or puncture wounds
- animal bites
- serious burns

Keep out of reach of children

- If swallowed, get medical help or contact a Poison Control Center right away

Directions

- apply as needed

Inactive Ingredient

Fragrance